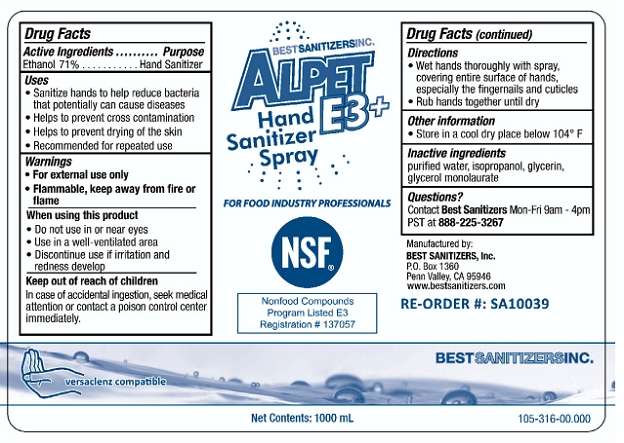 DRUG LABEL: Alpet E3 Plus Hand Sanitizer Spray
NDC: 59900-110 | Form: LIQUID
Manufacturer: Best Sanitizer, Inc.
Category: otc | Type: HUMAN OTC DRUG LABEL
Date: 20100305

ACTIVE INGREDIENTS: Ethanol 710 g/1000 mL

Drug Facts

Active Ingredient

Ethanol 71%

Purpose

Hand Sanitizer

Uses

- Sanitize hands to help reduce bacteria that potentially can cause disease
- Helps to prevent cross contamination
- Helps to prevent drying of the skin
- Recommended for repeated use

Warnings

- For external use only
- Flammable, keep away from fire or flame

When using this product

- Do not use in or near eyes
- Use in a well-ventilated area
- Discontinue use if irritation and redness develop

Keep out of reach of children

In case of accidental ingestion, seek medical attention or contact a poison control center immediately.

Directons

- Wet hands thoroughly with spray, covering entire surface of hands, especially the fingernails and cuticles
- Rub hands together until dry

Other information

- Store in a cool dry place below 104° F

Inactive ingredients

purified water, isopropanol, glycerin, glycerol monolaurate

Questions?

Contact Best Sanitizers Mon-Fri 9am - 4p PST at 888-225-3267

Principal Display Panel

NDC: 59900-110-02

NDC: 59900-110-03

NDC: 59900-110-04

NDC: 59900-110-05

NDC: 59900-110-06

NDC: 59900-110-07

NDC: 59900-110-08

Alpet E3 Plus Hand Sanitizer Spray

For Food Industry Professionals